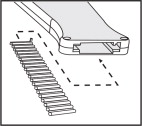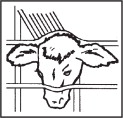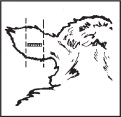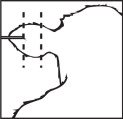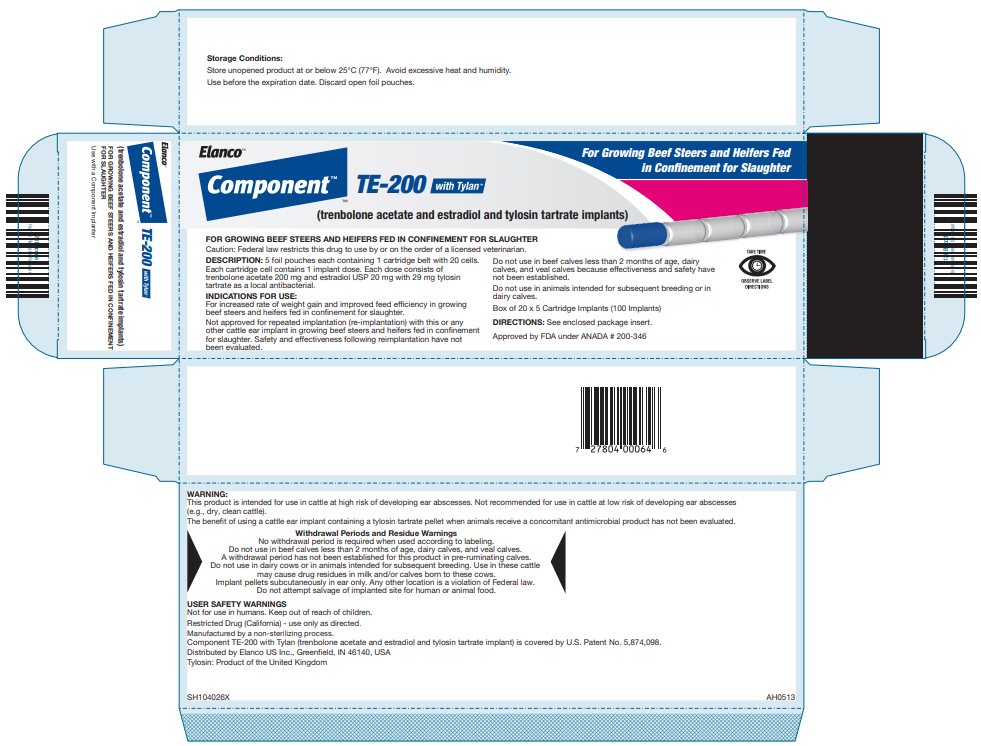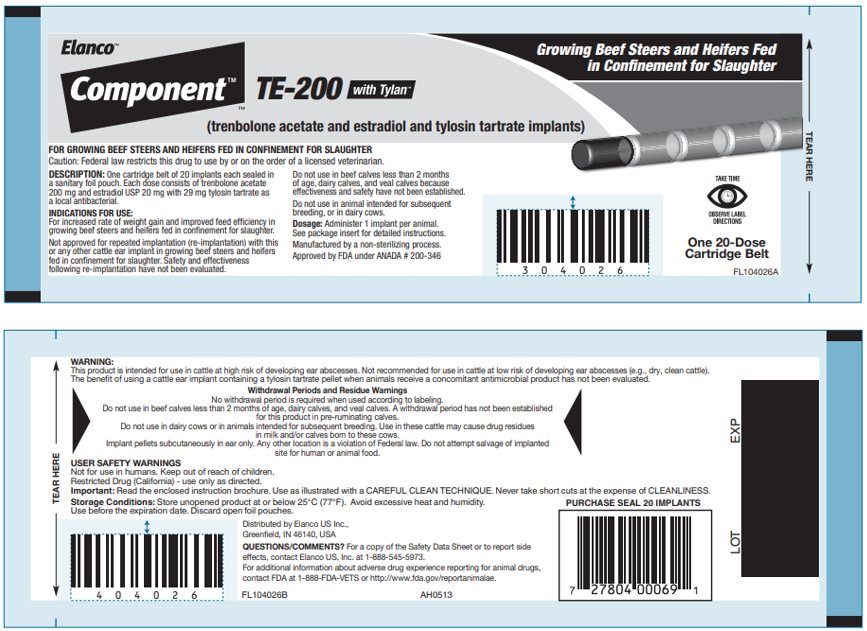 DRUG LABEL: Component TE-200 With Tylan
NDC: 58198-0513 | Form: IMPLANT
Manufacturer: Elanco US Inc.
Category: animal | Type: PRESCRIPTION ANIMAL DRUG LABEL
Date: 20251121

ACTIVE INGREDIENTS: trenbolone acetate 200 mg/1 1; estradiol 20 mg/1 1; tylosin tartrate 29 mg/1 1

Elanco™

Component™

TE-200 with TylanTM

(trenbolone acetate and estradiol and tylosin tartrate implants)

For Growing Beef Steers and Heifers Fed
in Confinement for Slaughter

FOR GROWING BEEF STEERS AND HEIFERS FED IN CONFINEMENT FOR SLAUGHTER

Caution: Federal law restricts this drug to use by or on the order of a licensed veterinarian.

20 dose Cartridge Belt

Use with a Component Implanter

DESCRIPTION:

Each cartridge belt holds 20 doses of Component TE-200 with Tylan (trenbolone acetate and estradiol and tylosin tartrate implant) Implants. Each dose of 11 pellets consists of 10 pellets containing a total of 200 mg of trenbolone acetate and 20 mg estradiol plus 1 pellet containing 29 mg tylosin tartrate as a local antibacterial.

INDICATIONS FOR USE:

For increased rate of weight gain and improved feed efficiency in growing beef steers and heifers fed in confinement for slaughter.

Not approved for repeated implantation (reimplantation) with this or any other cattle ear implant in growing beef steers and heifers fed in confinement for slaughter.

Do not use in beef calves less than 2 months of age, dairy calves, and veal calves because effectiveness and safety have not been evaluated.

Do not use in animals intended for subsequent breeding, or in dairy cows.

WARNING:

This product is intended for use in cattle at high risk of developing ear abscesses. Not recommended for use in cattle at low risk of developing ear abscesses (e.g., dry, clean cattle).
The benefit of using a cattle ear implant containing a tylosin tartrate pellet when animals receive a concomitant antimicrobial product has not been evaluated.

Withdrawal Periods and Residue Warnings
No withdrawal period is required when used according to labeling.
Do not use in beef calves less than 2 months of age, dairy calves, and veal calves. A withdrawal period has not been established for this product in pre-ruminating calves.
Do not use in dairy cows or in animals intended for subsequent breeding. Use in these cattle may cause drug residues in milk and/or calves born to these cows.
Implant pellets subcutaneously in ear only. Any other location is a violation of Federal law. Do not attempt salvage of implanted site for human or animal food.

USER SAFETY WARNINGS

Not for human use. Keep out of reach of children.

Restricted Drug (California) - use only as directed.

IMPLANTING INSTRUCTIONS:

Loading the Implanter
Load the implanter following the instructions supplied with each implanter.

Restrain the Animal

Speed of implantation as well as safety of handlers is best achieved by restraining animal in a squeeze chute using head restraint. When implanting horned cattle, better control is obtained with additional use of nose tongs.

Prepare the Implant Site

Scrub the back side of the ear (implant site) with a piece of clean absorbent cotton which has been soaked with topical germicidal solution. Follow manufacturer’s directions on germicide for correct strength and preparation of solution. Avoid getting disinfectant in animal’s eyes.

Where to Implant

The full contents of one cartridge cell should be implanted beneath the skin on the back side of the middle one-third of the ear illustrated in the drawing. The implant must not be closer to the head than the edge of the auricular cartilage ring farthest from the head. The location for insertion of the needle is a point toward the tip of the ear at least a needle length away from the intended deposition site. Avoid injuring the large arteries, veins and cartilage of the ear.

Insert the Needle

With one hand firmly grasp the ear. With the other hand insert needle point through the skin and ease forward on a lateral plane until the entire length of the needle is under the skin.

Implant the Pellets

After inserting the needle fully in the correct implant position, squeeze the trigger fully as the needle is withdrawn from the ear. This properly deposits the implant in the needle track. This procedure should prevent breakage or crushing of pellets if otherwise forced into contact with tough fibrous-tissue underlying the skin. The length and total contact area of a single dose are designed to permit absorption of the hormones after implantation to stimulate good weight gain. Broken or crushed pellets may interfere with rates of gain.

Storage Conditions

Store unopened product at or below 25°C (77°F). Avoid excessive heat and humidity.
Use before the expiration date printed on the foil pouch. Discard open foil pouches.

Approved by FDA under ANADA # 200-346

Manufactured by a non-sterilizing process.

Component TE-200 with Tylan (trenbolone acetate and estradiol and tylosin tartrate implants) is covered by U.S. Patent No. 5,874,098

Component, Tylan, Elanco and the diagonal bar logo are trademarks of Elanco or its affiliates.
© 2023 Elanco or its affiliates

Distributed by Elanco US Inc.,
Greenfield, IN 46140, USA

Tylosin: Product of the United Kingdom

QUESTIONS/COMMENTS? For a copy of the Safety Data Sheet or to report side effects, contact Elanco US, Inc. at 1-888-545-5973.
For additional information about adverse drug experience reporting for animal drugs, contact FDA at 1-888-FDA-VETS or http://www.fda.gov/reportanimalae.

April 2023

PA104026X AH0513

Principal Display Panel – Carton Label

Elanco™

Component™

TE-200 with Tylan™

(trenbolone acetate and estradiol and tylosin tartrate implants)

For Growing Beef Steers and Heifers Fed
in Confinement for Slaughter

Principal Display Panel – Cartridge Label

Elanco™

Component™

TE-200 with Tylan™

(trenbolone acetate and estradiol and tylosin tartrate implants)

Growing Beef Steers and Heifers Fed
in Confinement for Slaughter

One 20-Dose
Cartridge Belt